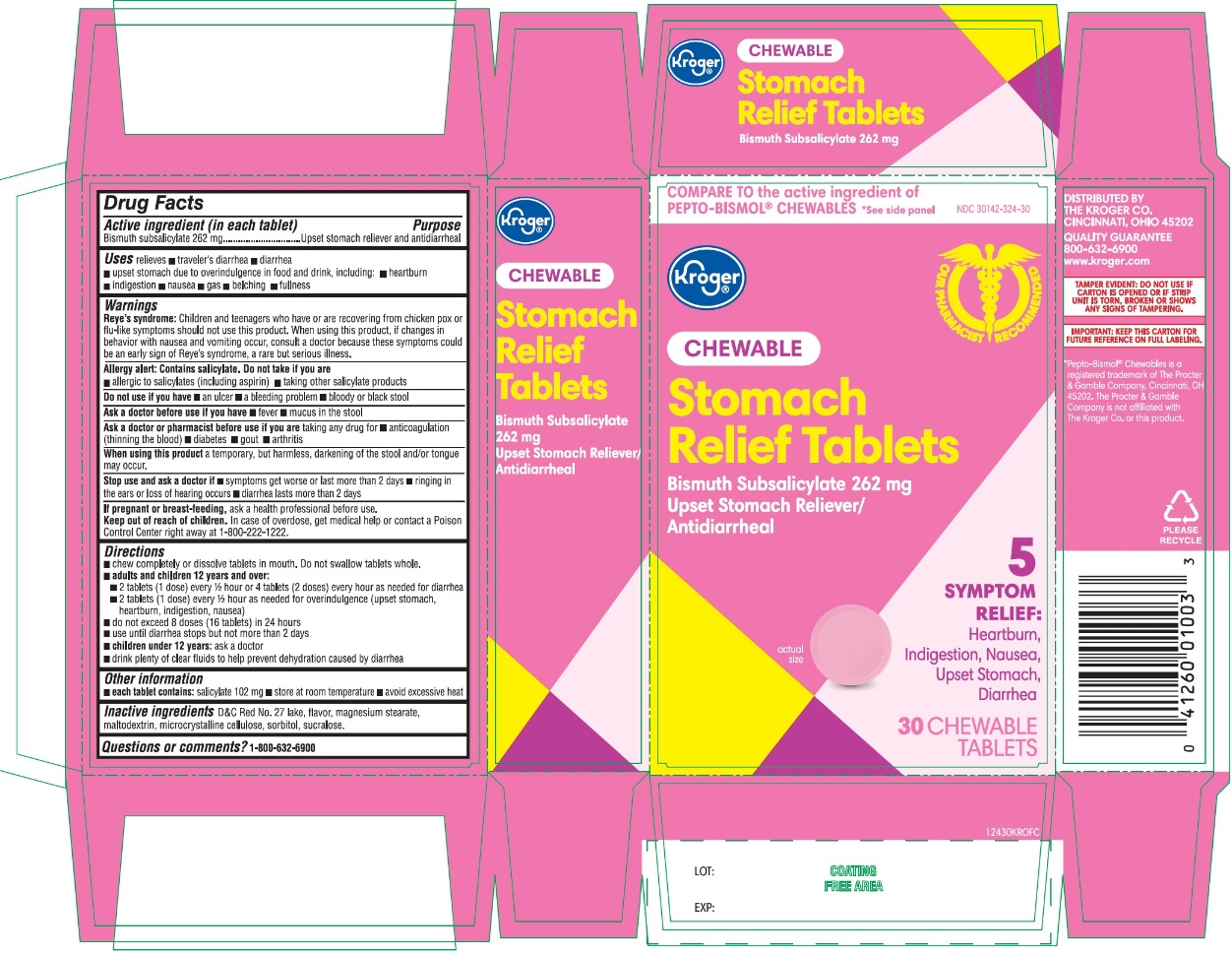 DRUG LABEL: Kroger Stomach Relief
NDC: 30142-324 | Form: TABLET, CHEWABLE
Manufacturer: KROGER COMPANY
Category: otc | Type: HUMAN OTC DRUG LABEL
Date: 20250804

ACTIVE INGREDIENTS: BISMUTH SUBSALICYLATE 262 mg/1 1
INACTIVE INGREDIENTS: D&C RED NO. 27; MAGNESIUM STEARATE; MALTODEXTRIN; MICROCRYSTALLINE CELLULOSE; SORBITOL; SUCRALOSE

Kroger Stomach Relief Bismuth Subsalicylate 30 Chewable Tablets

Active ingredient (in each tablet)

Bismuth subsalicylate 262 mg

Purpose

Upset stomach reliever and Anti-diarrheal

Uses

relieves:

- travelers’ diarrhea
- diarrhea
- upset stomach due to overindulgence in food and drink, including:
- heartburn
- indigestion
- nausea
- gas
- belching
- fullness

Warnings

Reye's syndrome:Children and teenagers who have or are recovering from chicken pox or flu-like symptoms should not use this product. When using this product, if changes in behavior with nausea and vomiting occur, consult a doctor because these symptoms could be an early sign of Reye's syndrome, a rare but serious illness.

Allergy alert: Contains salicylate. Do not take if you are

- allergic to salicylates (including aspirin)
- taking other salicylate products

Do not use if you have

- an ulcer
- a bleeding problem
- bloody or black stool

Ask a doctor before use if you have

- fever
- mucus in the stool

Ask a doctor or pharmacist before use if you aretaking any drug for

- anticoagulation (thinning of the blood)
- diabetes
- gout
- arthritis

When using this product

a temporary, but harmless, darkening of the stool and/or tongue may occur.

Stop use and ask a doctor if

- symptoms get worse or last more than 2 days
- ringing in the ears or loss of hearing occurs
- diarrhea lasts more than 2 days

If pregnant or breast-feeding,ask a health professional before use .

Keep Out of Reach of Children

In case of overdose, get medical help or contact a Poison Control Center immediately at 1-800-222-1222

Directions

- chew completely or dissolve tablets in mouth. Do not swallow tablets whole.
- adults and children 12 years and older:2 tablets (1 dose) every 1/2 hour or 4 tablets (2 doses) every hour as needed for diarrhea
- 2 tablets (1 dose) every 1/2 hour as needed for overindulgence (upset stomach, heartburn, indigestion, nausea)
- do not exceed 8 doses (16 tablets) in 24 hours
- use until diarrhea stops but not more than 2 days
- children under 12 years:ask a doctor
- drink plenty clear fluids to help prevent dehydration caused by diarrhea.

Other information

- each tablet contains: salicylate 102 mg
- store at room temperature.
- avoid excessive heat
- keep this carton for future reference on full labeling

TAMPER EVIDENT: DO NOT USE IF CARTON IS OPENED OR IF STRIP UNIT IS TORN, BROKEN OR SHOWS ANY SIGNS OF TEMPERING.

Inactive ingredients

D&C Red No. 27 lake, flavor, magnesium stearate, maltodextrin, microcrystalline cellulose, sorbitol, sucralose.

Questions or comments?

1-800-632-6900

Principal Display

NDC# 30142-324-30

COMPARE TO the active ingredient of PEPTO-BISMOL®CHEWABLES *See side panel

CHEWABLE

Stomach Relief Tablets

Bismuth Subsalicylate 262 mg

Upset Stomach, Reliever / Antidiarrheal

5 SYMPTOM RELIEF

- Heartburn
- Indigestion
- Nausea
- Upset Stomach
- Diarrhea

Original Flavor

30 CHEWABLE TABLETS

DISTRIBUTED BY:

THE KROGER CO.

CINCINNATI, OHIO 45202

QUALITY GUARANTEE

800-632-6900

IMPORTANT: KEEP THIS CARTON FOR FUTURE REFERENCE ON FUL LABELING.

*Pepto-Bismol®Chewable is a registered trademark of The Procter & Gamble Company, Cincinnati, OH 45202. The Procter & Gamble Company is not affiliated with The Kroger Co. or this product.